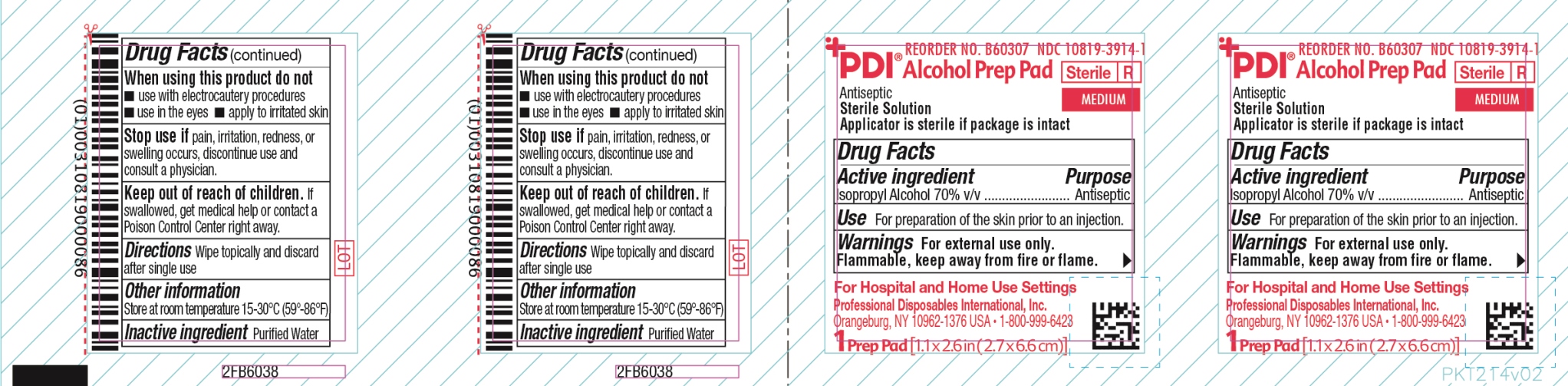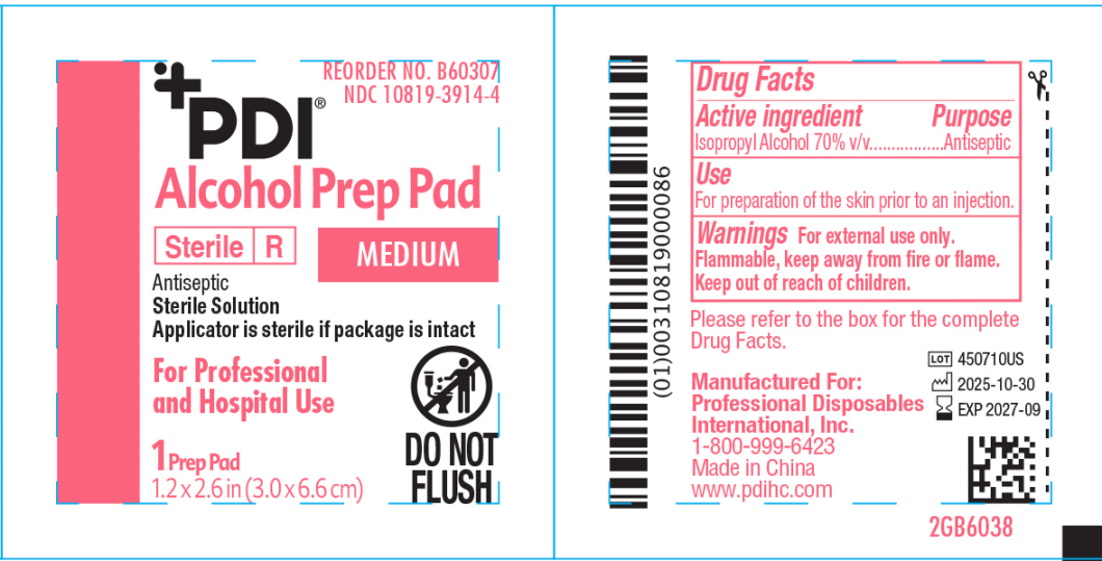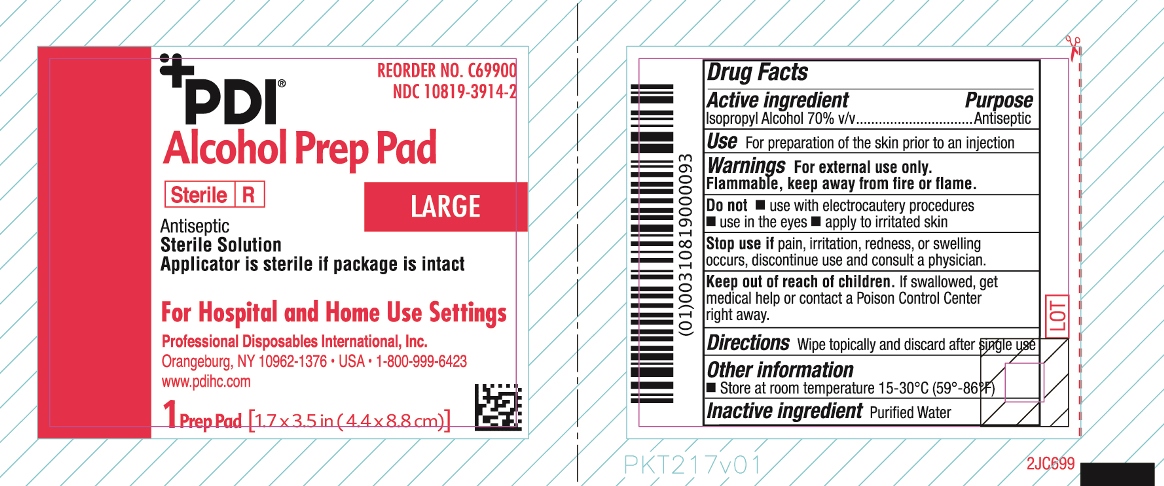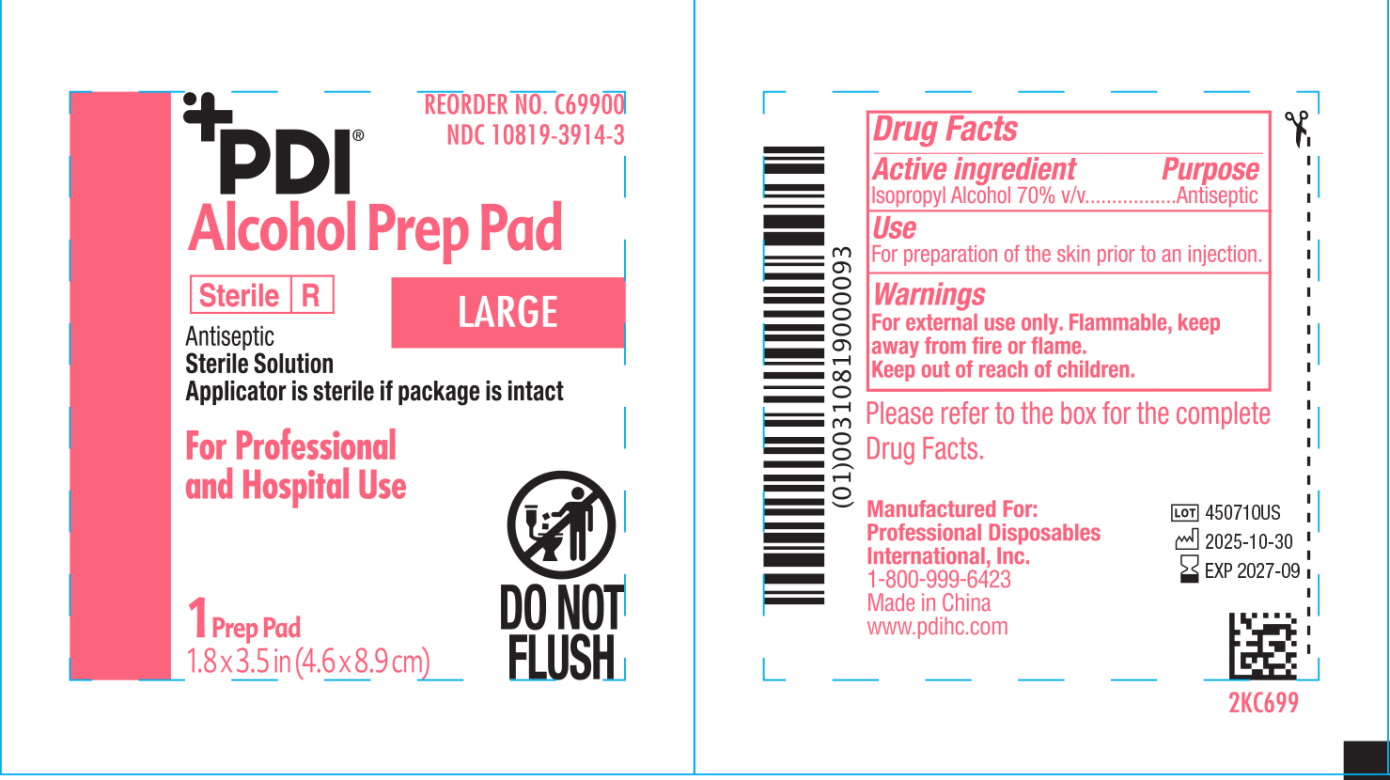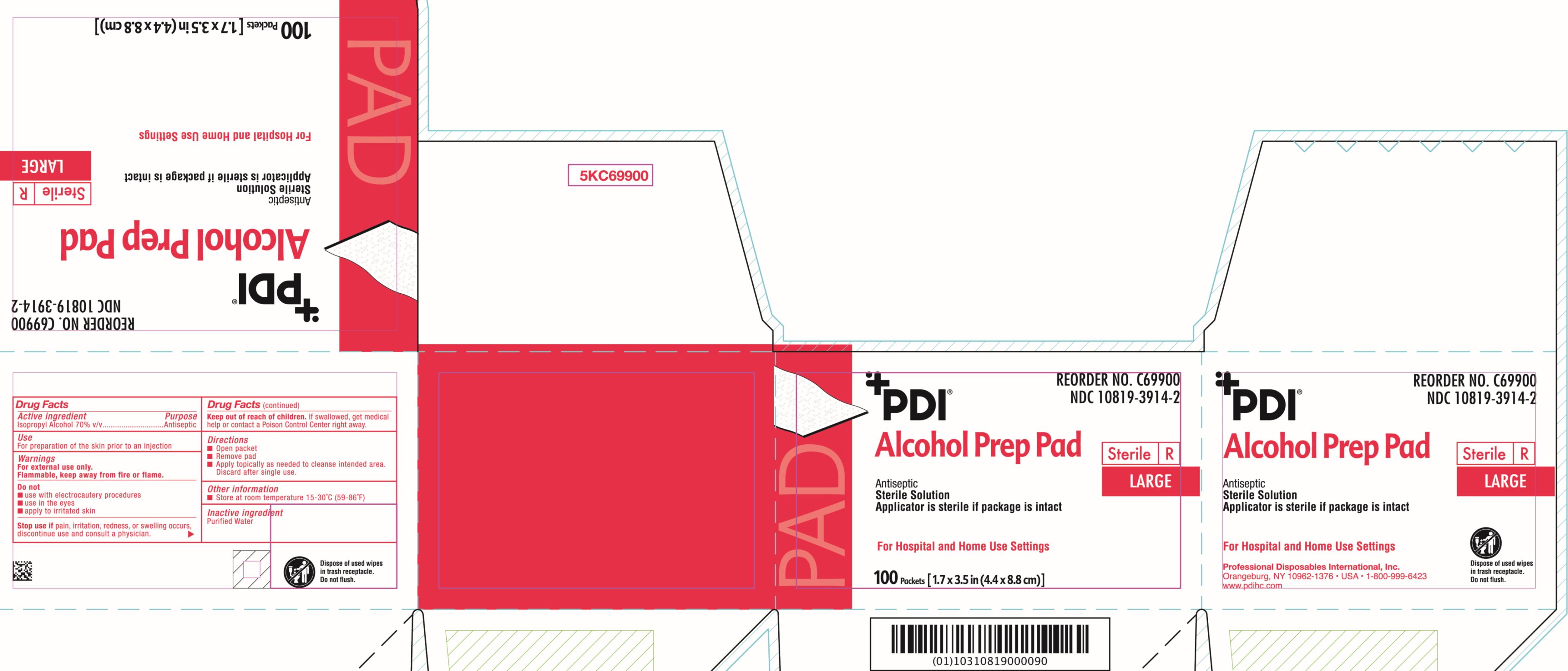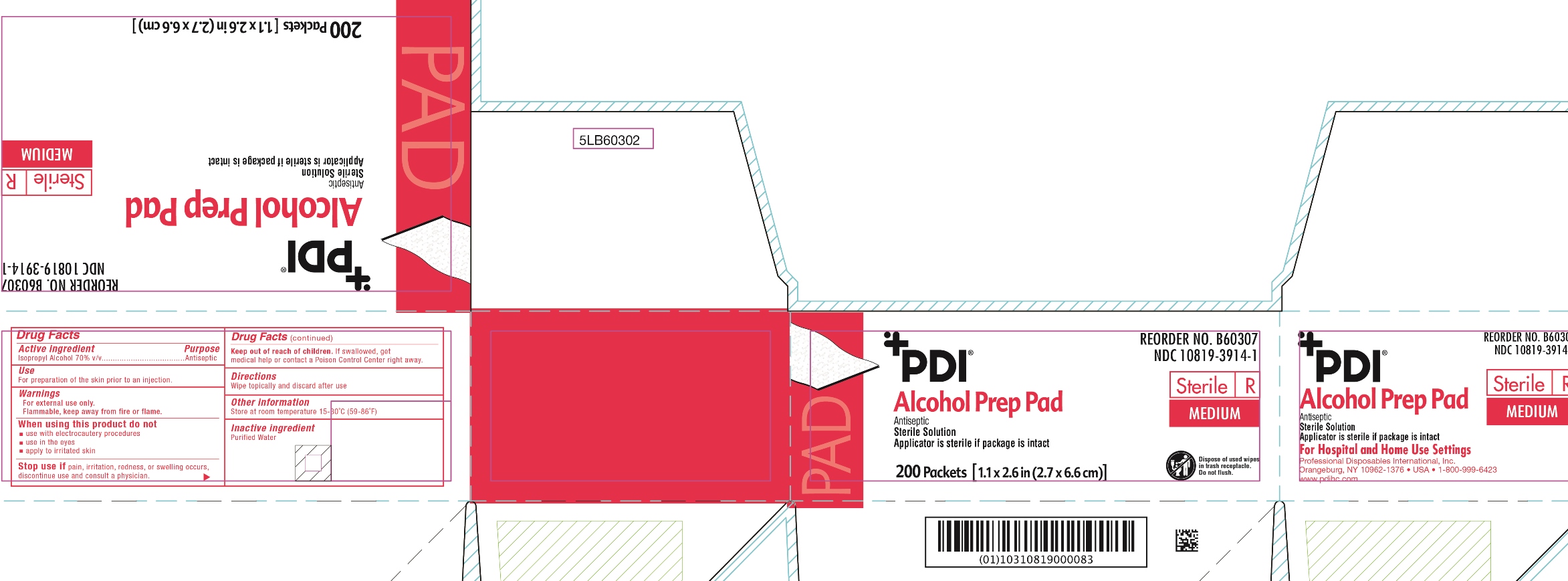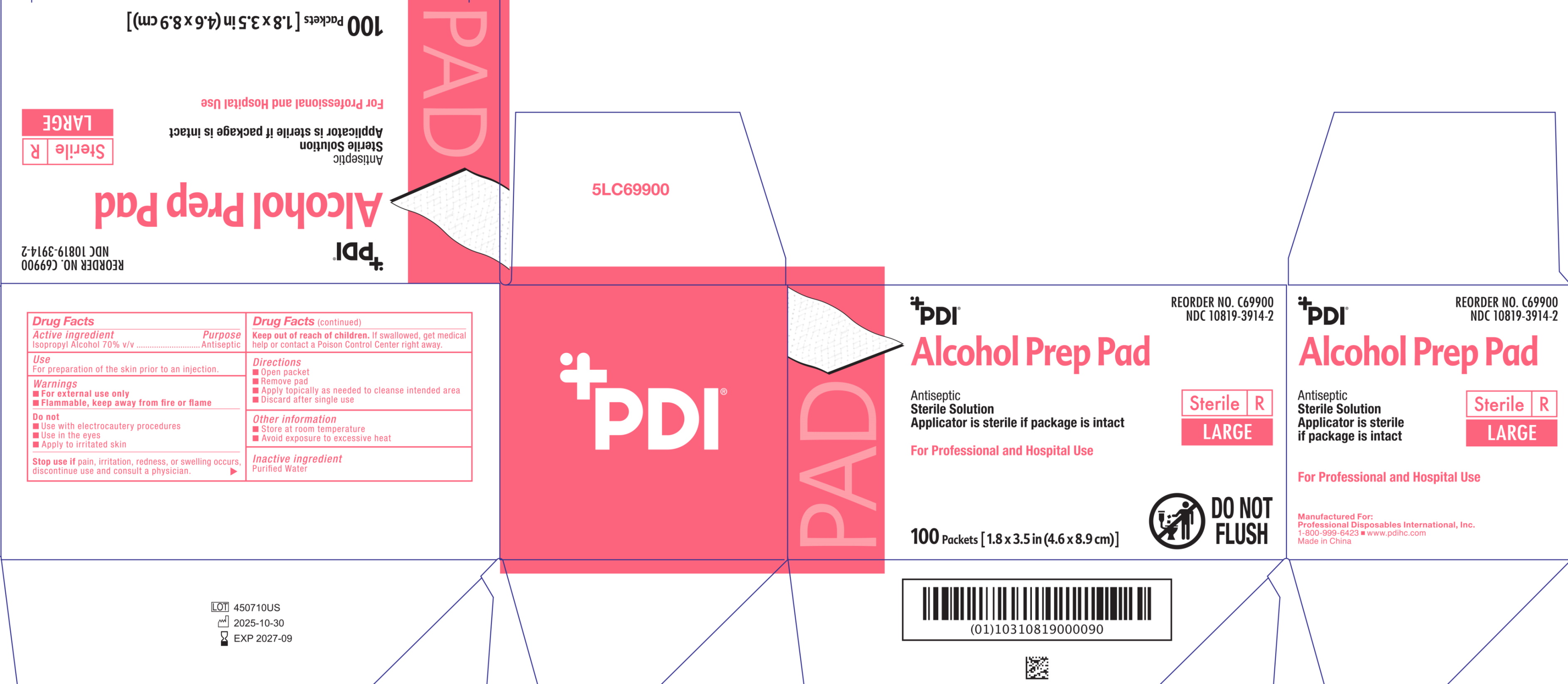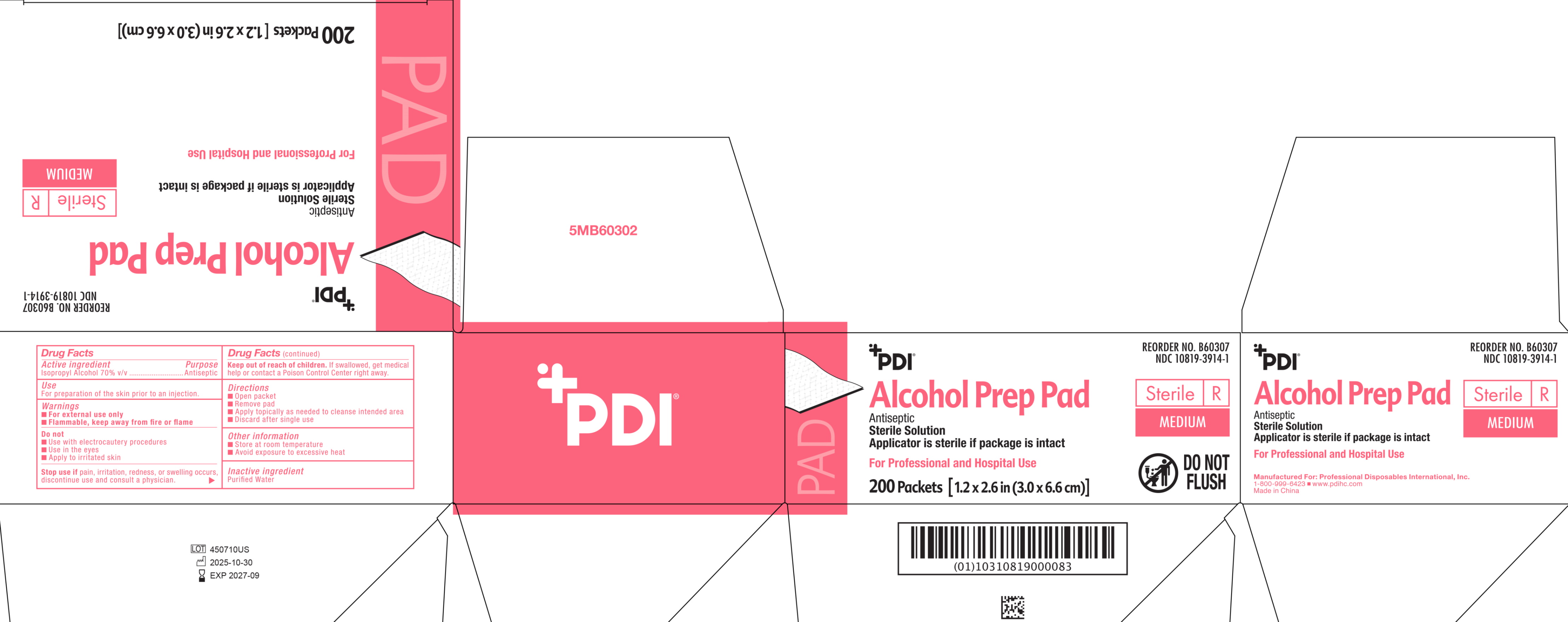 DRUG LABEL: PDI Alcohol Prep Pad Sterile
NDC: 10819-3914 | Form: CLOTH
Manufacturer: Professional Disposables International Inc
Category: otc | Type: HUMAN OTC DRUG LABEL
Date: 20260218

ACTIVE INGREDIENTS: ALCOHOL 0.7 mL/1 mL
INACTIVE INGREDIENTS: WATER 0.3 mL/1 mL

Sterile Alcohol NDC 10819-3914
10819-3914-1 Med B60307 box
10819-3914-2 Large C69900 box
10819-3914-3 Large C69900 packet
10819-3914-4 Med B60307 packet

Active ingredient

Isopropyl Alcohol 70% v/v

Purpose

Antiseptic

Use

For preparation of the skin prior to an injection

Warnings

For external use only.

Flammable, keep away from fire or flame.

Do not

- use with electrocautery preocedures
- use in the eyes
- apply on irritated skin

Stop use if

pain, irritation, redness or swelling occurs. discontinue use and consult a physician.

Keep out of reach of children

If swallowed,get medical help or contact a Poison Control Center right away.

Directions

- Open packet
- Remove pad
- Apply topically as needed to cleanse intended area
- Discard after single use

Other information

- Store at room temperature
- Avoid exposure to excessive heat

Inactive ingredient

Purified Water

Principal display panel

Medium Web:

Medium Box:

Large Web:

Large Box: